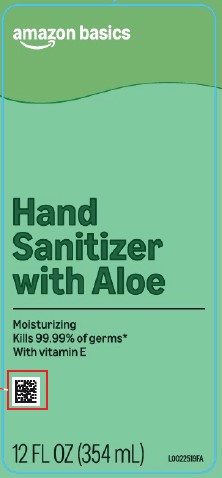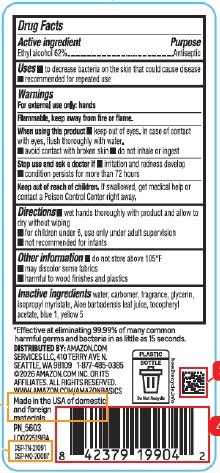 DRUG LABEL: Alcohol
NDC: 72288-826 | Form: LIQUID
Manufacturer: Amazon.com Services LLC
Category: otc | Type: HUMAN OTC DRUG LABEL
Date: 20260216

ACTIVE INGREDIENTS: ALCOHOL 62 mL/100 mL
INACTIVE INGREDIENTS: WATER; CARBOMER INTERPOLYMER TYPE A (ALLYL SUCROSE CROSSLINKED); GLYCERIN; ISOPROPYL MYRISTATE; ALOE; TOCOPHEROL; FD&C BLUE NO. 1; FD&C YELLOW NO. 5

Basics 826.000/826AA rev 1
Moisturizing Hand Sanitizer with Aloe

Active ingredient

Ethyl Alcohol 62%

Purpose

Antiseptic

Uses

- to decrease bacteria on the skin that could cause disease
- recommended for repeated use

Warnings

For external use only: hands

Flammable, keep away from fire or flame.

When using this product

- keep out of eyes. In case of contact with eyes, flush thoroughly with water
- avoid contact with broken skin
- do not inhale of ingest

Stop use and ask a doctor if

- irritation and redness develop
- condition persists for more than 72 hours

Keep out of reach of children.

If swallowed, get medical help or contact a Poison Control Center right away.

Directions

- wet hands thoroughly with product and allow to dry without wiping
- for children under 6, use only under adult supervision
- not recommended for infants

Other information

- do not store above 105° F
- may discolor some fabrics
- harmful to wood finishes and plastics

Inactive ingredients

water, carbomer, fragrance, glycerin, isopropyl myristate, Aloe barbadensis leaf juice, tocopheryl acetate, blue 1, yellow 5

Claims

*Effective at eliminating 99.99% of many common harmful germs and bacteria in as little as 15 seconds.

Made in the USA of domestic and foreign components.

Adverse Reaction

DISTRIBUTED BY: Amazon.com Services LLC, 410 Terry Ave. N.

Seattle, WA 98109 1-877-485-0385

©2026 Amazon.com, Inc. or its affiliates. All rights reserves.

www.amazon.com/amazonbasics

DSP-TN-21091

DSP-MO-20087

PLASTIC BOTTLE

Do Not Recycle

how2recycle.info

Principal display panel

amazon basics

Hand Sanitizer with Aloe

Moisturizing

Kills 99.99% of germs*

With vitamin E

12 FL OZ (354 mL)